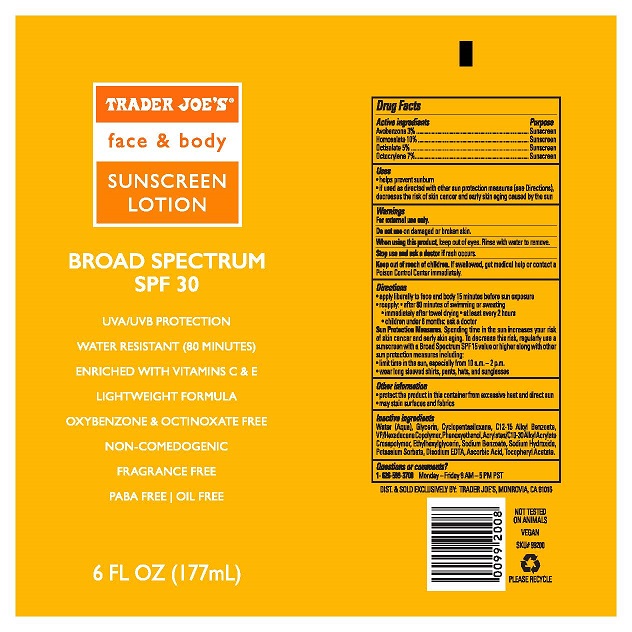 DRUG LABEL: TRADER JOES FACE AND BODY SUNSCREEN
NDC: 71270-153 | Form: LOTION
Manufacturer: Trader Joe's Company
Category: otc | Type: HUMAN OTC DRUG LABEL
Date: 20241022

ACTIVE INGREDIENTS: AVOBENZONE 3 g/100 mL; HOMOSALATE 10 g/100 mL; OCTISALATE 5 g/100 mL; OCTOCRYLENE 7 g/100 mL
INACTIVE INGREDIENTS: GLYCERIN; CYCLOMETHICONE 5; ALKYL (C12-15) BENZOATE; VINYLPYRROLIDONE/HEXADECENE COPOLYMER; PHENOXYETHANOL; CARBOMER INTERPOLYMER TYPE A (ALLYL SUCROSE CROSSLINKED); ETHYLHEXYLGLYCERIN; SODIUM BENZOATE; SODIUM HYDROXIDE; POTASSIUM SORBATE; EDETATE DISODIUM; ASCORBIC ACID; .ALPHA.-TOCOPHEROL ACETATE; WATER

TRADER JOE’S (as PLD) - FACE AND BODY SUNSCREEN LOTION (71270-153)

ACTIVE INGREDIENT

AVOBENZONE 3%

HOMOSALATE 10%

OCTISALATE 5%

OCTOCRYLENE 7%

PURPOSE

SUNSCREEN

USES

- HELPS PREVENT SUNSCREEN
- IF USED AS DIRECTED WITH OTHER SUN PROTECTION MEASURES (SEE DIRECTIONS), DECREASES THE RISK OF SKIN CANCER AND EARLY SKIN AGING CAUSED BY THE SUN.

WARNINGS

For external use only.

Do not useon damaged or broken skin.

When using this product, keep out of eyes. Rinse with water to remove.

Stop use and ask a doctorif rash occurs.

Keep out of reach of children.If swallowed, get medical help or contact a Poison Control Center immediately.

DIRECTIONS

- Apply liberally to face and body 15 minutes before sun exposure.
- Reapply: after 80 minutes of swimming or sweating
- immediately after towel drying
- at least every 2 hours.
- Children under 6 months: ask a doctor.

Sun Protection Measures.Spending time in the sun increases your risk of skin cancer and early skin aging. To decrease this risk, regularly use a sunscreen with a Broad Spectrum SPF 15 value or higher along with other sun protection measures including:

- limit time in the sun, especially from 10 a.m. – 2 p.m.
- wear long sleeved shirts, pants, hats and sunglasses.

OTHER INFORMATION

- Protect the product in this container from excessive heat and direct sun
- May stain surfaces and fabrics.

INACTIVE INGREDIENTS

WATER (AQUA), GLYCERIN, CYCLOPENTASILOXANE, C12-15 ALKYL BENZOATE, VP/HEXADECENE COPOLYMER, PHENOXYETHANOL, ETHYLHEXYLGLYCERIN, SODIUM BENZOATE, SODIUM HYDROXIDE, POTASSIUM SORBATE, DISODIUM EDTA, ASCORBIC ACID, TOCOPHERYL ACETATE.

QUESTIONS OR COMMENTS?

1- 626-599-3700Monday – Friday 9 AM – 5 PM PST